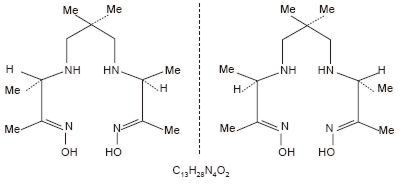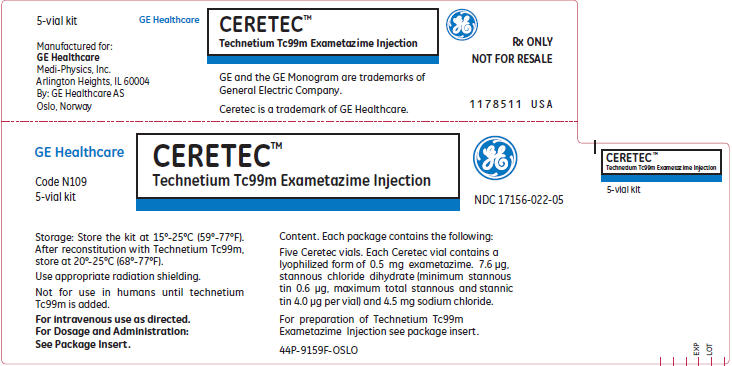 DRUG LABEL: CERETEC
NDC: 17156-022 | Form: INJECTION, POWDER, LYOPHILIZED, FOR SOLUTION
Manufacturer: Medi-Physics Inc. dba GE Healthcare.
Category: prescription | Type: HUMAN PRESCRIPTION DRUG LABEL
Date: 20240110

ACTIVE INGREDIENTS: TECHNETIUM TC-99M EXAMETAZIME 0.5 mg/5 mL
INACTIVE INGREDIENTS: Stannous Chloride 7.6 ug/5 mL; Sodium Chloride 4.0 mg/5 mL; Nitrogen

Ceretec™ N109A
Kit for the Preparation of Technetium Tc99m Exametazime Injection

Diagnostic Radiopharmaceutical

For intravenous use only

DESCRIPTION

The Ceretec kit is supplied as a pack of 5 vials for use in the preparation of a technetium Tc99m exametazime intravenous injection as a diagnostic radiopharmaceutical for use as an adjunct in the detection of altered regional cerebral perfusion and for the radiolabeling of autologous leukocytes. Each vial of Ceretec contains a pre-dispensed sterile, non-pyrogenic, lyophilized mixture of 0.5 mg exametazime [(RR,SS)-4.8-diaza-3,6,6,9-tetramethylundecane-2, 10-dione bisoxime], 7.6 µg stannous chloride dihydrate (minimum stannous tin 0.6 µg; maximum total stannous and stannic tin 4.0 µg per vial) and 4.5 mg sodium chloride, sealed under nitrogen atmosphere with a rubber closure. The product contains no antimicrobial preservative.

Prior to publication of the USAN, exametazime was formerly known as hexamethylpropylene amine oxime (HM-PAO). The name HM-PAO appears in many publications.

The structural formula of exametazime is:

When sterile pyrogen-free sodium pertechnetate Tc99m in isotonic saline is added to the vial of Ceretec, a Tc99m complex of exametazime is formed.

Administration is by intravenous injection for diagnostic use.

Physical Characteristics

Technetium Tc99m decays by isomeric transition with a physical half-life of 6.03 hours.(1) Photons that are useful for imaging studies are listed in Table 1.

Table 1. Principal Radiation Emission Data-technetium Tc99m
Radiation | Mean %/ Disintegration | Mean Energy (keV)
Gamma 2 | 87.87 | 140.5
(1) Dillman, L.T. and Von der Lage, F.C. Radionuclide decay schemes and nuclear parameters for use in radiation-dose estimation. MIRD Phamphlet No. 10, p. 62, 1975.

External Radiation

The specific gamma ray constant for technetium Tc99m is 206 microCoulomb kg-1/37 MBq-h, (0.8 R/millicurie-h) at 1 cm. The first half-value thickness of lead (Pb) for technetium Tc99m is 0.2 mm. A range of values for the relative attenuation of the radiation emitted by this radionuclide that results from interposition of various thicknesses of Pb is shown in Table 2. For example, the use of a 2.7 mm thickness of Pb will decrease the external radiation exposure by a factor of 1,000.

Table 2. Radiation Attenuation by Lead Shielding
Shield Thickness (Pb) mm | Coefficient of Attenuation
0.2 | 0.5
0.95 | 10^–1
1.8 | 10^–2
2.7 | 10^–3
3.6 | 10^–4
4.5 | 10^–5

To correct for physical decay of this radionuclide, the fractions that remain at selected intervals relative to the time of calibration are shown in Table 3.

Table 3. Physical Decay Chart: Tc99m half-life 6.03 hours
Hours | Fraction Remaining | Hours | Fraction Remaining
0 [Calibration time (time of preparation)] | 1.000 | 7 | 0.447
1 | 0.891 | 8 | 0.399
2 | 0.795 | 9 | 0.355
3 | 0.708 | 10 | 0.317
4 | 0.631 | 11 | 0.282
5 | 0.563 | 12 | 0.252
6 | 0.502 | 24 | 0.063

CLINICAL PHARMACOLOGY

General

When technetium Tc99m pertechnetate is added to exametazime in the presence of stannous reductant, a lipophilic technetium Tc99m complex is formed. This lipophilic complex is the active moiety. It converts at approximately 12%/hour to less lipophilic species. When the secondary complex is separated from the lipophilic species, it is unable to cross the blood-brain-barrier. The useful life of the reconstituted agent is limited to 30 minutes.

Pharmacokinetics

Studies in normal volunteers have shown that the technetium Tc99m complex of the RR,SS(d,l) diastereoisomer of exametazime is rapidly cleared from the blood after intravenous injection. Uptake in the brain reaches a maximum of 3.5-7.0% of the injected dose within one minute of injection. Up to 15% of the activity is eliminated from the brain by 2 minutes post injection, after which little activity is lost for the following 24 hours except by physical decay of technetium Tc99m. The activity not associated with the brain is widely distributed throughout the body, particularly in muscle and soft tissue. About 30% of the injected dose is found in the gastrointestinal tract immediately after injection and about 50% of this is excreted through the intestinal tract over 48 hours. Also, about 40% of the injected dose is excreted through the kidneys and urine over the 48 hours after injection.

Leukocyte

The lipophilic Tc99m exametazime complex is taken up by leukocytes, and selectively retained in neutrophils. Label elution rate is up to 10% in the first hour.

Pharmacodynamics

Tc99m-labeled leukocyte: Based upon in vivo recovery and very low lung and liver uptake, the labeled leukocytes are still functional. Following reinjection of the Tc99m labeled leukocytes the circulating granulocyte activity as a percentage of labeled granulocyte activity at 40 minutes after injection gave a mean of 37% (range 10-47%).

During the first hour following injection of Tc99m labeled leukocytes, activity is seen in the lungs, liver, spleen, blood pool, bone marrow and the bladder. The kidneys (parenchyma and/or renal pelvis) and gall bladder may also be visualized. Over the first 1-6 hours, the Tc99m is visualized in the bowel. At 24 hours post-injection substantial colonic activity is seen. The normal areas visualized in earlier scans are still visible.

CLINICAL TRIALS

Two clinical trials were performed in a total of 88 patients who had suspected intra-abdominal infection or inflammation. Subjects received both Tc99m labeled leukocytes and In-111 labeled leukocytes. Images were obtained at 2 and 30 minutes and at 2 and 4 hours and 24 hours. In two other clinical trials, in a total of 127 patients with suspected abdominal inflammation or infection received Tc99m labeled leukocytes. Imaging was at 24 hours in one study and at 1, 3 and 24 hours in the other. In all 4 studies, images were blindly evaluated and the findings were confirmed by surgery, biopsy or other clinical data.

Based on the above 4 studies, between 2 to 4 hours Tc99m labeled leukocytes had 95-100% sensitivity and 62-85% specificity with similar numbers of false positive and false negative findings. The value of the 24 hour Tc99m labeled leukocyte images is inconsistent. In all studies the false positive and false negatives relate to the bowel background, the location of the site of infection/inflammation and whether or not it is contiguous with the bowel. The 24 hour films should be interpreted with great caution because of a high bowel background; false negatives were noted in both Tc99m and In-111 labeled leukocytes.

Other studies suggest that the interpretation of the images could be affected by the presence of tumors, infarction and peritonitis, etc. Liver abscess may be missed because of the bowel background. Caution should be exercised in making the final diagnosis.

INDICATIONS AND USAGE

Technetium Tc99m exametazime scintigraphy may be useful as an adjunct in the detection of altered regional cerebral perfusion in stroke.

Tc99m exametazime is indicated for leukocyte labeled scintigraphy as an adjunct in the localization of intra-abdominal infection and inflammatory bowel disease.

CONTRAINDICATIONS

None known.

PRECAUTIONS

As with any injected product, acute hypersensitivity or allergic reactions are possible. Limited reports have been received of hypersensitivity reactions following administration of Tc99m labeled leukocytes prepared using Tc99m exametazime. However, the materials used in leukocyte cell separation may cause hypersensitivity reactions. It is essential that cells are washed free of sedimentation agents before they are reinjected into the patient.

In case of side effects following administration of radiopharmaceuticals, users should ensure the availability of appropriate medical treatment at the time of administration of any radiopharmaceutical to the patient.

A thorough knowledge of the normal distribution of intravenously administered technetium Tc99m exametazime injection is essential in order to interpret pathologic studies accurately. Caution should be exercised in making the final diagnosis. Results can be affected by the presence of tumor, infarction, peritonitis, non-gastrointestinal or bony sites of inflammatory cell collections.

The contents of the Ceretec vial are not radioactive. After the sodium pertechnetate Tc99m is added, the product is radioactive and adequate shielding of the final preparation must be maintained. The contents of the Ceretec vial are intended only for use in preparation of technetium Tc99m exametazime injection and are NOT to be administered directly to the patient.

General

The contents of the Ceretec vial are sterile and pyrogen free. The vial contains no bacteriostatic preservative. It is essential that the user follow the directions carefully and adhere to strict aseptic procedures during preparation of the radiopharmaceutical.

Radiopharmaceuticals should be used only by or under the control of physicians who are qualified by training and experience in the safe use and handling of radionuclides and whose experience and training have been approved by the appropriate governmental agency authorized to license the use of radionuclides.

To minimize radiation dose to the bladder, the patient should be encouraged to void when the examination is completed and as often thereafter as possible. Adequate hydration should be encouraged to permit frequent voiding.

Carcinogenesis, Mutagenesis, Impairment of Fertility

Long term animal studies have not been performed to evaluate carcinogenic potential or whether exametazime affects fertility in males or females. When evaluated in the Ames test, exametazime increased the apparent rate of gene mutation in the TA100 strain of S. typhimurium. Exametazime did not cause chromosomal aberrations in vitro (Chinese Hamster Ovary cells) or in vivo (rat bone marrow).

Pregnancy Category C

Animal reproduction studies have not been conducted with Tc99m exametazime. It is also not known whether Tc99m exametazime can cause fetal harm when administered to a pregnant woman or if it can affect reproductive capacity. Therefore, Tc99m exametazime should not be administered to a pregnant woman unless the potential benefit justifies the potential risk to the fetus.

Nursing Mothers

Technetium Tc99m is excreted in human milk during lactation. It is not known whether exametazime is excreted in human milk. Therefore, formula feedings should be substituted for breast feeding for 60 hours.

Pediatric Use

Safety and effectiveness in pediatric patients have not been established.

Geriatric Use

Clinical studies of Ceretec™ did not include sufficient numbers of subjects aged 65 and over to determine whether they respond differently from younger subjects. Other reported clinical experience has not identified differences in responses between the elderly and younger patients. In general, dose selection for an elderly patient should be cautious, usually starting at the low end of the dosing range, reflecting the greater frequency of decreased hepatic, renal or cardiac function, and of concomitant disease or other drug therapy.

This drug is known to be substantially excreted by the kidney, and the risk of toxic reactions to this drug may be greater in patients with impaired renal function. Because elderly patients are more likely to have decreased renal function, care should be taken in dose selection, and it may be useful to monitor renal function.

ADVERSE REACTIONS

Rash with generalized erythema, facial edema and fever has been reported in less than 1% of patients. A transient increase in blood pressure was seen in 8% of patients.

DOSAGE AND ADMINISTRATION

Tc99m labeled leukocytes for adjunctive localization of intra-abdominal infection or inflammation.

The normal adult (70 kg) dose is 0.259-0.925 GBq (7-25 mCi) as Tc99m labeled leukocytes by intravenous injection. Optimal planar imaging is between 2-4 hours.

Cerebral Scintigraphy

The recommended dose range for i.v. administration, of reconstituted sodium pertechnetate Tc99m exametazime in the average adult (70 kg) is 370-740 MBq (10-20 mCi).

Dynamic imaging may be performed between 0 to 10 minutes following injection. Static imaging may be performed from 15 minutes up to 6 hours after injection.

INSTRUCTIONS FOR PREPARATION AND USE

GENERAL PREPARATION PRECAUTIONS

The technetium Tc99m labeling reaction involved in preparing technetium Tc99m exametazime injection depends on maintaining tin in the divalent (reduced) state. Any oxidant present in the sodium pertechnetate Tc99m employed may adversely affect the quality of the preparation. Sodium pertechnetate Tc99m containing oxidants should not be used for the preparation of the labeled product. To meet the last requirement, a generator must be eluted within 24 hours prior to obtaining any elute for reconstitution with the Ceretec kit.

Sodium Chloride Injection, USP must be used as the diluent. Do not use bacteriostatic sodium chloride as a diluent for sodium pertechnetate Tc99m injection because it will increase the oxidation products and adversely affect the biological distribution of Ceretec.

The contents of the Ceretec vial are sterile and pyrogen free. The vial contains no bacteriostatic preservative. It is essential that the user follow the directions carefully and adhere to strict aseptic procedures during preparation of the radiopharmaceutical.

Technetium Tc99m exametazime injection, like other radioactive drugs, must be handled with care and appropriate safety measures should be used to minimize radiation exposure to clinical personnel. Care should also be taken to minimize radiation exposure to the patient consistent with proper patient management.

Care should be taken when handling blood specimens to be labeled using this radiopharmaceutical. Even if the subject has been tested, no method can offer complete assurance that Hepatitis B Virus, Human Immuno-deficiency Virus (HIV) or other infectious agents are absent. All human blood samples should be considered potentially infectious. Precautions for handling are as those for handling radioactive materials.

Procedure for the Preparation of Technetium Tc99m Exametazime Injection

Note: Sterile technique must be used throughout. The user should wear waterproof gloves during the handling and administration procedure.

1) Place one of the vials in a suitable shielding container and sanitize the rubber septum with an isopropyl alcohol swab.
2) Using a 10 mL syringe, inject into the shielded vial 5 mL of sterile eluate from a technetium Tc99m generator (see cautionary notes 1-3). Before withdrawing the syringe from the vial, withdraw 5 mL of gas from the space above the solution to normalize the pressure in the vial. Gently invert the shielded vial for 10 seconds to ensure complete dissolution of the powder.
3) Assay the total activity and calculate the volume to be injected. The patient dose should be measured in a suitable radioactivity calibration system immediately prior to administration.
4) Complete the label provided and attach to the vial shield. The technetium Tc99m exametazime injection is ready for quality control.
5) Maintain adequate shielding of the radioactive preparation.
6) Do not use the preparation more than 30 minutes after time of formulation. Discard any unused material.
7) Visually inspect the reconstituted material at a safe distance behind lead glass, and do not use if there is evidence of foreign matter.
8) The injection may be prepared for use in cerebral scintigraphy or for use in the preparation of Tc99m labeled white blood cells (WBCs).
9) The pH of the prepared injection is 9.0-9.8.
10) Also see section on Cautionary Notes for all Preparations.

Procedure for Radiolabeling of Autologous Leukocytes with Technetium Tc99m Exametazime Injection

Note: Sterile technique must be used throughout. The user should wear waterproof gloves during the handling and administration procedure.

1) Prepare a 60 mL syringe containing 10 mL acid citrate dextrose solution.
2) Using aseptic venipuncture technique and the prepared syringe (from Step 1) fitted with a 19 or 20 gauge needle, withdraw approximately 40 mL whole blood from the patient. (Blood withdrawal should be smooth and slow so as not to produce bubbles or foaming). Cap syringe after withdrawing blood.
3) Gently mix the contents of the syringe.
4) Clamp the syringe barrel to the ring stand in an upright (needle side up) position and tilt the syringe 10-20 degrees from its position perpendicular to the bench.
5) Allow the red cells to sediment 30-60 minutes, depending upon when the supernatant [leukocyte rich plasma (LRP)] looks clear of red blood cells.
6) Replace the capped needle with a winged infusion set.
7) Collect the plasma LRP into a centrifuge tube marked WBC by expressing the LRP through the infusion set tubing assuring the red cells do not enter the container.
8) Immediately centrifuge the capped WBC tube at 400-450 g for 5 minutes.
9) Transfer the supernatant to the leukocyte poor plasma (LPP) tube allowing enough supernatant to cover the white cell button.
  (Note: the button often contains a small number of red cells and may appear red.) Reserve LPP for later use (steps 12, 16, 19).
10) Wash the white cell button with approximately 5.0 mL Sodium Chloride Injection, USP (0.9%). Cap the tube and resuspend the button by gently swirling.
11) Centrifuge the capped WBC tube at 150 g for 8 minutes and discard all but 0.5-1.0 mL of the supernate to cover the cells.
12) Add 1.0 mL of LPP to the white cell button and resuspend the cells by gentle swirling.
13) Reconstitute a vial of Ceretec with approximately 30 mCi of Tc99m pertechnetate in 5.0 mL Sodium Chloride (0.9%) Injection, according to the procedure outlined below. Generator eluate more than 2 hours old should not be used. Parenteral drug products should be inspected visually for particulate matter and discoloration before administration.
14) Add the Tc99m Ceretec to the WBC tube. Swirl gently to mix.
15) Set a lab timer for 15 minutes and allow the white cells to incubate. Swirl periodically during the incubation.
16) After incubation, withdraw about 10 mL of the LPP and add to the white cell suspension in the WBC tube.
17) Cap the WBC tube, gently swirl, and then centrifuge at 450 g for 5 minutes.
18) Decant the supernatant in the WBC tube into the wash tube and leave the labeled white cells in the WBC tube.
19) Add approximately 5 mL of LPP to the WBC tube. Resuspend the cells by gentle swirling.
20) When the cells are in suspension, withdraw the cells into a syringe. Cap the syringe and assay the amount of radioactivity in a dose calibrator.
21) Place the syringe in a lead shielded container.
22) Administer the Tc99m labeled leukocyte suspension using a 19G needle as soon as possible after labeling.
23) Also see section of Cautionary Notes for all Preparations.

Cautionary Notes for all Preparations

1) 0.37 GBq up to 2.00 GBq (10 mCi up to 54 mCi) technetium Tc99m may be added to the vial. Before reconstitution the technetium Tc99m generator eluate may be adjusted to the correct radioactive concentration to a volume of 5 mL by dilution with preservative-free, non-bacteriostatic saline for injection.
2) Use only eluate from a technetium Tc99m generator which was previously eluted within 24 hours. Generator eluate more than 2 hours old should not be used. For the highest radiochemical purity reconstitute with freshly eluted technetium Tc99m generator eluate. When reconstituting a vial of Ceretec with 31 to 54 mCi, generator eluate more than 30 minutes old should not be used.
3) Radiochemical purity testing must be performed prior to patient administration. A radiochemical purity greater than 80% is necessary for product acceptance.
4) Do not use the final radiopharmaceutical preparation more than 30 minutes after the time of reconstitution. Discard any unused material.

Quality Control

Radiochemical purity determination must be performed before administration to the patient. Three potential radiochemical impurities may be present in the prepared injection of the lipophilic technetium Tc99m exametazime complex.

These are a secondary technetium Tc99m exametazime complex, free pertechnetate, and reduced-hydrolyzed-technetium Tc99m. A combination of 3 chromatographic systems is necessary for the complete definition of the radiochemical composition of the injection.

The following protocol has been designed to enable analysis of the radiochemical purity of Ceretec (99mTc-exametazime). It should be started within 2 minutes of reconstitution. The entire procedure takes approximately 15 minutes.

Equipment and Eluents

1) Quality control kit which includes all necessary components
2) Individual supplies:
  SA ITLC strips 20 cm × 2.0 cm
  Whatman No. 1 strips 6 cm × 0.7 cm
  MEK (methyl ethyl ketone [butanone]) (99.9 + % HPLC Grade)
  0.9% aqueous sodium chloride (non-bacteriostatic)
  50% aqueous acetonitrile (99.9 + % HPLC Grade)
  Dilute with non-bacteriostatic Water for Injection
  Glass test tubes (12 × 75 mm)
  Glass measuring cylinders (100ml) with covers
  1 mL syringes with 25 gauge needles
3) Suitable counting equipment.

Method

1) Prepare one chromatography tube containing 0.2-0.3 mL of 50% acetonitrile. Prepare two 100 ml cylinders each containing a 1 cm depth of fresh MEK and 0.9% sodium chloride, respectively. Identify the solvent in each cylinder.
2) Prepare two SA ITLC strips and one Whatman No. 1 paper strip. Mark the Whatman strip 1.0 cm from the bottom as the point of origin. Mark the SA ITLC strips 2.5cm from the bottom as the point of origin. Mark both the SA ITLC strips at 14 cm above the origin (solvent front).
3) Reconstitute a Ceretec vial according to this insert.
4) Apply at least 5 µL samples of Ceretec to the origin of the 3 strips within 15 minutes of reconstitution. Immediately place one SA ITLC strip into the MEK tank, the second SA ITLC strip into the saline tank and the Whatman No. 1 paper strip into the 50% acetonitrile tube. Make sure strips are not adhering to the sides of the container.
5) The SA ITLC MEK strip takes approximately 15 minutes to run. When the eluate has reached the solvent front mark remove the strip from the tube with forceps and immediately cut 1.0 cm above the origin.
6) The SA ITLC saline strip takes approximately 15 minutes to run. When the eluate has reached the solvent front mark remove the strip from the tube with forceps and immediately cut 2.5 cm above the origin.
7) The Whatman No. 1 paper CH3CN strip takes approximately 100 seconds to run. When the eluate has reached the solvent front remove the strip from the tube with forceps and immediately cut 0.5 cm above the origin.
8) Count the separate sections of each strip to determine the activity distribution. Make sure proper counting geometry is maintained attempting to reduce any interference from equipment dead time.
9) Determine:
  % bottom of saline strip – % bottom of MEK strip
  (= % lipophilic exametazime complex)
  % top of saline strip (= % pertechnetate)
  % bottom of Whatman No. 1 paper strip (= % reduced-hydrolyzed-Tc)
  A radiochemical purity of >80% may be expected provided the measurement has been carried out within 4 hours of reconstitution for stabilized Ceretec and 30 minutes for Ceretec used for WBC labeling.

Interpretation of Chromatogram

System 1 (SA ITLC: MEK [butanone])

Secondary Tc exametazime complex and reduced-hydrolyzed-Tc remain at the origin.

Lipophilic Tc exametazime complex and pertechnetate migrate at Rf 0.8-1.0.

System 2 (SA ITLC: 0.9% sodium chloride)

Lipophilic-Tc exametazime complex, secondary Tc exametazime complex and reduced-hydrolyzed-Tc remain at the origin. Pertechnetate migrates at Rf 0.8-1.0.

System 3 (Whatman No. 1 1: 50% aqueous acetonitrile)

Reduced-hydrolyzed-Tc remains at the origin. Lipophilic Tc exametazime complex, secondary Tc exametazime complex and pertechnetate migrate at Rf 0.8-1.0.

RADIATION DOSIMETRY

Based on human data, the absorbed radiation doses to an average human adult (70 kg) from an intravenous injection of this product are estimated below. The values are listed as µGy/MBq, rads/mCi with urination every 2 hours. Bladder wall dose is 19 µGy/MBq, 0.07 rads/mCi with 4 hour urination and 89 µGy/MBq, 0.33 rads/mCi with no urination.

Table 4. Estimated Absorbed Radiation Dose [Data supplied by Oak Ridge Associated Universities, Radiopharmaceutical Internal Dose Information Center.] for Cerebral Scintigraphy
Target Organ | Absorbed radiation dose Tc99m exametazime injection
Target Organ | µGy/MBq | rads/mCi | mGy/740 MBq | rads/20 mCi
Lachrymal Glands | 69.4 | 0.258 | 51.36 | 5.16
Gallbladder Wall | 51.0 | 0.19 | 37.74 | 3.80
Kidney | 35.0 | 0.13 | 25.90 | 2.60
Thyroid | 27.0 | 0.10 | 19.98 | 2.00
Upper Large | 21.0 | 0.079 | 15.54 | 1.58
Intestine Wall
Liver | 15.0 | 0.054 | 11.10 | 1.08
Small Intestine Wall | 12.0 | 0.044 | 8.88 | 0.88
Lower Large | 15.0 | 0.054 | 11.10 | 1.08
Intestine Wall
Urinary Bladder Wall | 13.0 | 0.047 | 9.62 | 0.94
Brain | 6.9 | 0.026 | 5.11 | 0.52
Ovaries | 6.3 | 0.023 | 4.66 | 0.46
Testes | 1.8 | 0.007 | 1.33 | 0.14
Whole Body | 3.6 | 0.013 | 2.66 | 0.26
Red Marrow | 3.4 | 0.013 | 2.52 | 0.26
Bone Surfaces | 4.8 | 0.018 | 3.55 | 0.36
Eyes | 6.9 | 0.026 | 5.11 | 0.52

Table 5. In vivo Localization of Tc99m Labeled Leukocytes
The estimated absorbed radiation doses to various organs following the intravenous administration of Tc99m labeled leukocytes given by ICRP 53 [International Commission on Radiological Protection, "Radiation Dose to Patients from Radiopharmaceuticals", ICRP 53, 1988.] are as follows (bladder voiding every 3.5 hours)
Target Organ | Absorbed Radiation Dose
Target Organ | (mGy per 200 MBq) | rads/25 mCi
Spleen | 30 | 13.89
Red Marrow | 4.4 | 2.04
Liver | 4 | 1.85
Pancreas | 2.8 | 1.3
Ovaries | 0.84 | 0.39
Testes | 0.34 | 0.16
Uterus | 0.76 | 0.35
Effective Dose Equivalent (EDE) 3.4 mSv/200 MBq.

HOW SUPPLIED

The kit comprises 5 individual vials of sterile, non-pyrogenic, freeze-dried mixture of exametazime, stannous chloride dihydrate and sodium chloride, 5 radiation labels, 5 radiochemical purity worksheets, 5 labeling efficiency worksheets, 1 leukocyte labeling schematic and 1 package insert.

NDC 17156-022-05

Storage

Store the kit at 15°-25°C (59°-77°F).

Store the formulated drug for up to 30 minutes at 20°-25°C (68°-77°F) using appropriate radiation shielding.

This reagent kit is approved for use by persons licensed by the Illinois Emergency Management Agency pursuant to 32 Ill. Code Adm. Section, Section 330.260(a) and 335.4010 or under equivalent licenses of the U.S. Nuclear Regulatory Commission, or an Agreement State.

Patent No. 4,789,736

Distributed by:
GE Healthcare
Medi-Physics, Inc.
Arlington Heights, IL 60004

Customer Service:
1-800-292-8514
Professional Services:
1-800-654-0118

Manufactured by:
GE Healthcare AS
Oslo, Norway

Ceretec is a trademark of GE Healthcare.

GE and the GE Monogram are trademarks of General Electric Company.

© 2013 General Electric Company – All rights reserved.

43P-9159F-OSLO

Revised March 2013

PRINCIPAL DISPLAY PANEL - 5 Vial Kit

GE Healthcare

CERETEC™
Technetium Tc99m Exametazime Injection

Code N109
5-vial kit

NDC 17156-022-05

Storage: Store the kit at 15°-25°C (59°-77°F).
After reconstitution with Technetium Tc99m,
store at 20°-25°C (68°-77°F).

Use appropriate radiation shielding.

Not for use in humans until technetium
Tc99m is added.

For intravenous use as directed.
For Dosage and Administration:
See Package Insert.

Content. Each package contains the following:

Five Ceretec vials. Each Ceretec vial contains a
lyophilized form of 0.5 mg exametazime. 7.6 μg,
stannous chloride dihydrate (minimum stannous
tin 0.6 μg, maximum total stannous and stannic
tin 4.0 μg per vial) and 4.5 mg sodium chloride.

For preparation of Technetium Tc99m
Exametazime Injection see package insert.

44P-9159F-OSLO